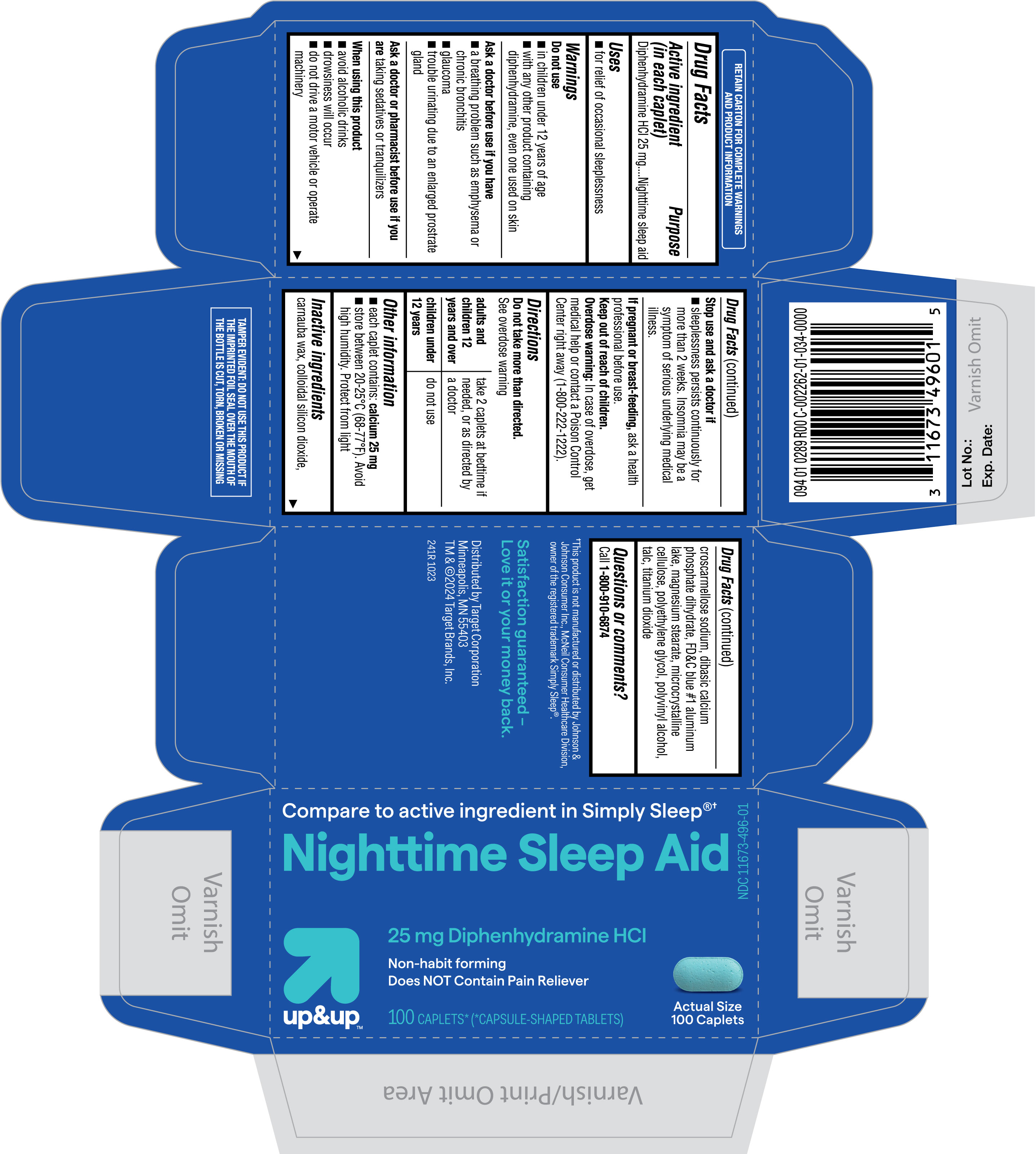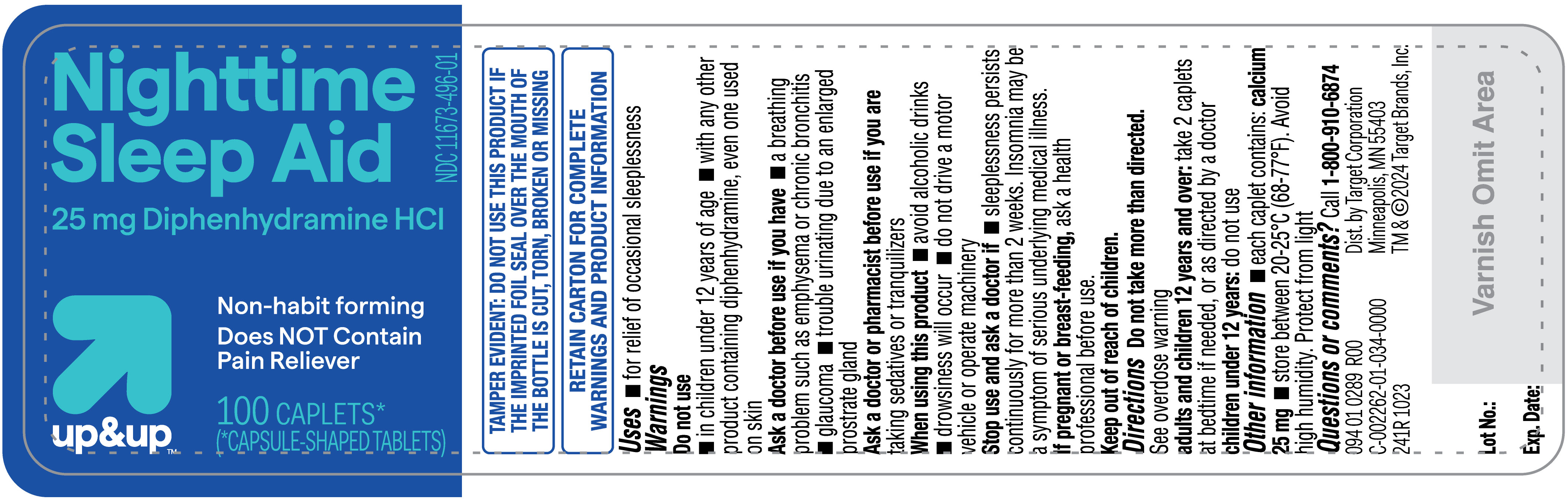 DRUG LABEL: Nighttime Sleep Aid
NDC: 11673-496 | Form: TABLET
Manufacturer: TARGET CORPORATION
Category: otc | Type: HUMAN OTC DRUG LABEL
Date: 20231216

ACTIVE INGREDIENTS: DIPHENHYDRAMINE HYDROCHLORIDE 25 mg/1 1
INACTIVE INGREDIENTS: SILICON DIOXIDE; MAGNESIUM STEARATE; POLYVINYL ALCOHOL, UNSPECIFIED; TITANIUM DIOXIDE; CARNAUBA WAX; FD&C BLUE NO. 1 ALUMINUM LAKE; DIBASIC CALCIUM PHOSPHATE DIHYDRATE; POLYETHYLENE GLYCOL, UNSPECIFIED; CROSCARMELLOSE SODIUM; MICROCRYSTALLINE CELLULOSE; TALC

Target Nighttime Sleep-aid Diphenhydramine Hydrochloride 25 mg Tablets

Active ingredient (in each caplet)

Diphenhydramine HCl 25 mg

Purpose

Nighttime sleep aid

Uses

■ for relief of occasional sleeplessness

Warnings

Do not use

■ in children under 12 years of age
■ with any other product containing diphenhydramine, even one used on skin

Ask a doctor before use if you have

■ a breathing problem such as emphysema or chronic bronchitis
■ glaucoma
■ trouble urinating due to an enlarged prostrate gland

Ask a doctor or pharmacist before use if you are

taking sedatives or tranquilizers

When using this product

■ avoid alcoholic drinks
■ drowsiness will occur
■ do not drive a motor vehicle or operate machinery

Stop use and ask a doctor if

■ sleeplessness persists continuously for more than 2 weeks. Insomnia may be a symptom of serious underlying medical illness.

If pregnant or breast-feeding,

ask a health professional before use.

Keep out of reach of children.

Overdose warning: In case of overdose, get medical help or contact a Poison Control Center right away (1-800-222-1222).

Directions

Do not take more than directed.
See overdose warning

adults and children 12 years and over | take 2 caplets at bedtime if needed, or as directed by a doctor
children under 12 years | do not use

Other information

■ each caplet contains: calcium 25 mg
■ store between 20-25°C (68-77°F). Avoid high humidity. Protect from light

Inactive ingredients

carnauba wax, colloidal silicon dioxide, croscarmellose sodium, dibasic calcium phosphate dihydrate, FD&C blue #1 aluminum lake, magnesium stearate, microcrystalline cellulose, polyethylene glycol, polyvinyl alcohol, talc, titanium dioxide

Questions or comments?

Call 1-800-910-6874